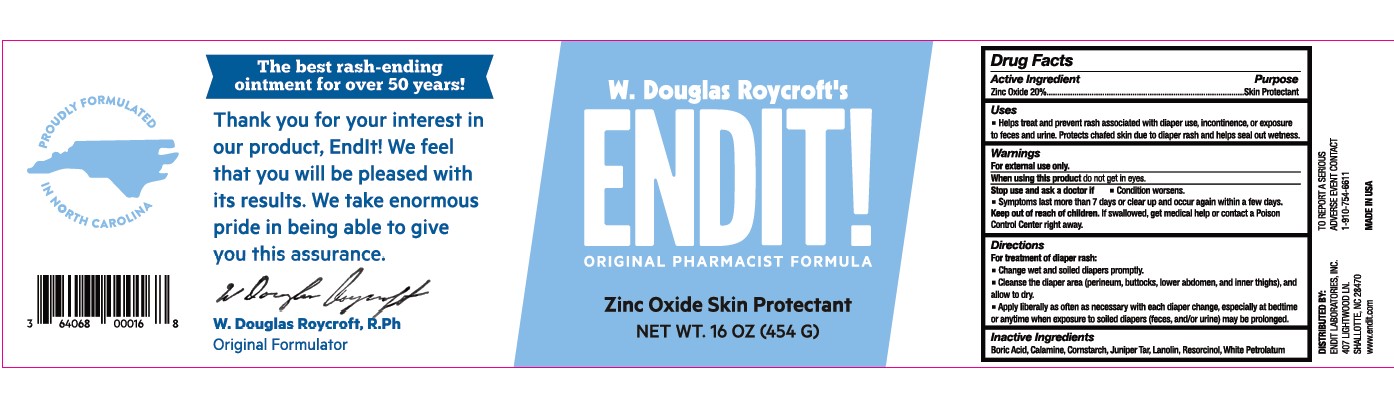 DRUG LABEL: Endit Zinc Oxide Skin Protectant
NDC: 64068-402 | Form: OINTMENT
Manufacturer: Endit Laboratories, Inc.
Category: otc | Type: HUMAN OTC DRUG LABEL
Date: 20231215

ACTIVE INGREDIENTS: ZINC OXIDE 20 g/100 g
INACTIVE INGREDIENTS: BORIC ACID; FERRIC OXIDE RED; STARCH, CORN; JUNIPER TAR; LANOLIN; RESORCINOL; PETROLATUM

Endit! Zinc Oxide Skin Protectant

Active Ingredient:

Zinc Oxide 20.00%

Purpose:

Skin Protectant

Uses:

Helps treat and prevent rash associated with diaper use, incontinence, or exposure to feces and urine. Protects chafed skin due to diaper rash and helps seal out wetness.

Warnings:

For external use only.

do not get in eyes. When using this product

Stop use and ask doctor if

Condition worsens.

Symptoms last more than 7 days or clear up and occur again within a few days.

Keep out of reach of children. If swallowed, get medical help or contact a Poison Control Center right away.

Directions:

- Change wet and soiled diapers promptly.
- Cleanse the diaper area (perineum, buttocks, lower abdomen, and inner thighs), and allow to dry.
- Apply liberally as often as necessary with each diaper change, especially at bedtime or anytime when exposure to soiled dapers (feces, and/or urine) may be prolonged.

Other Ingredients:

Boric Acid, Calamine, Cornstarch, Juniper Tar, Lanolin, Resorcinol, White Petrolatum